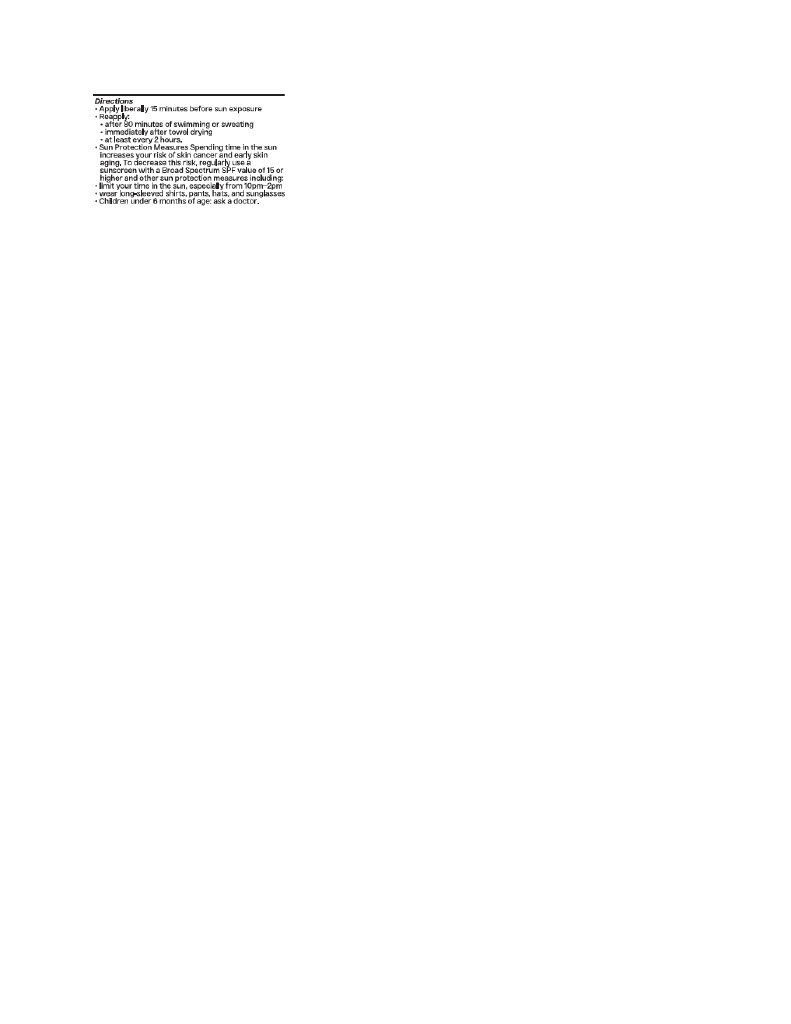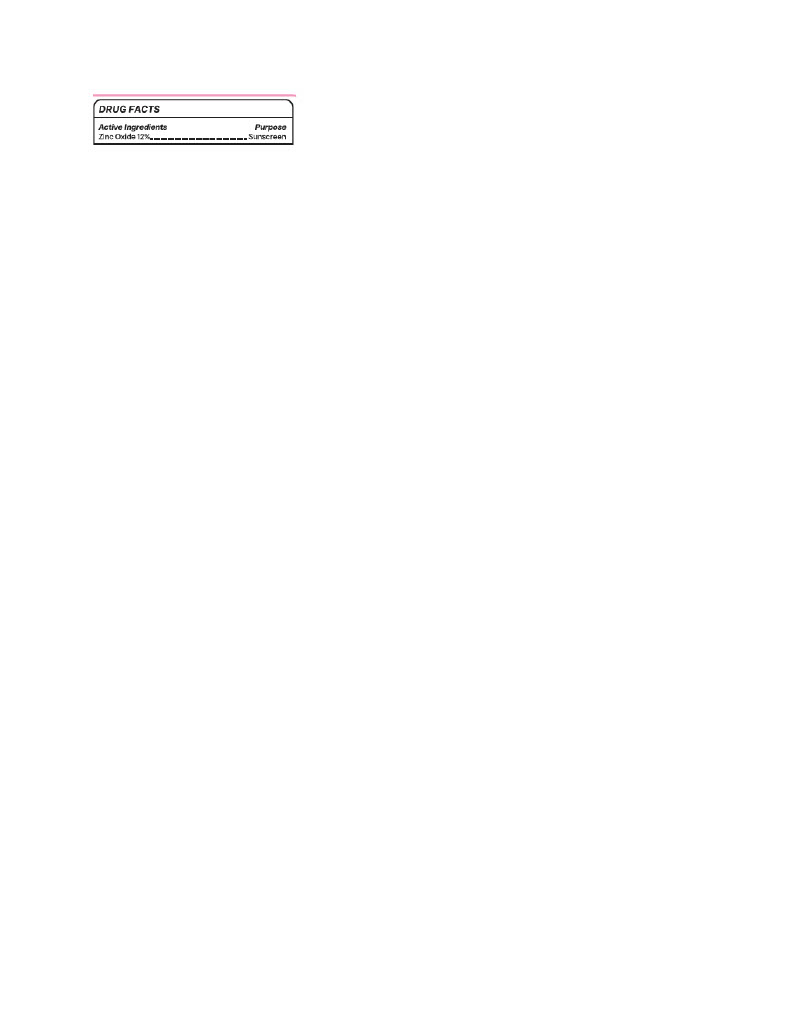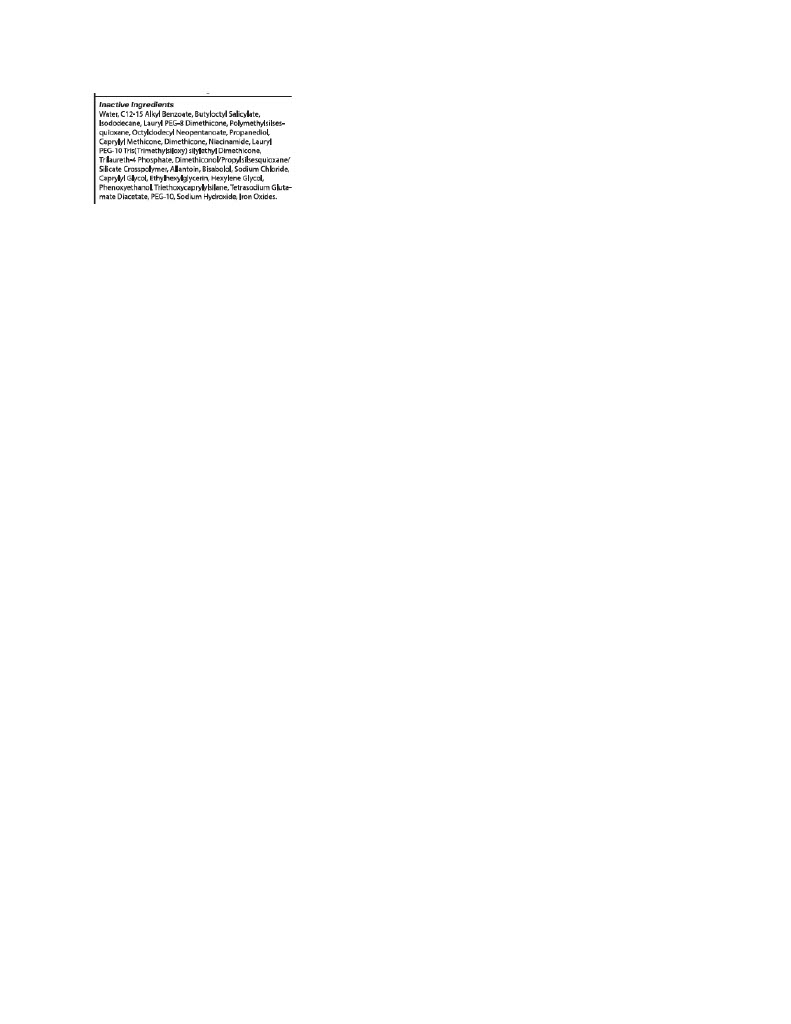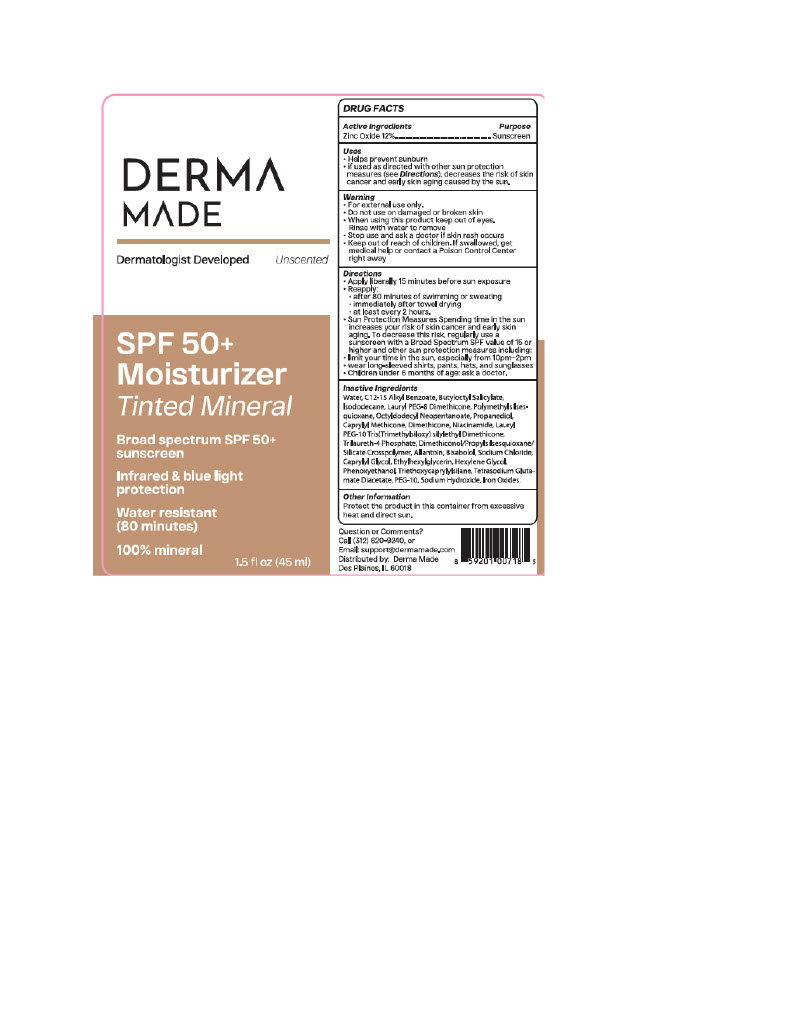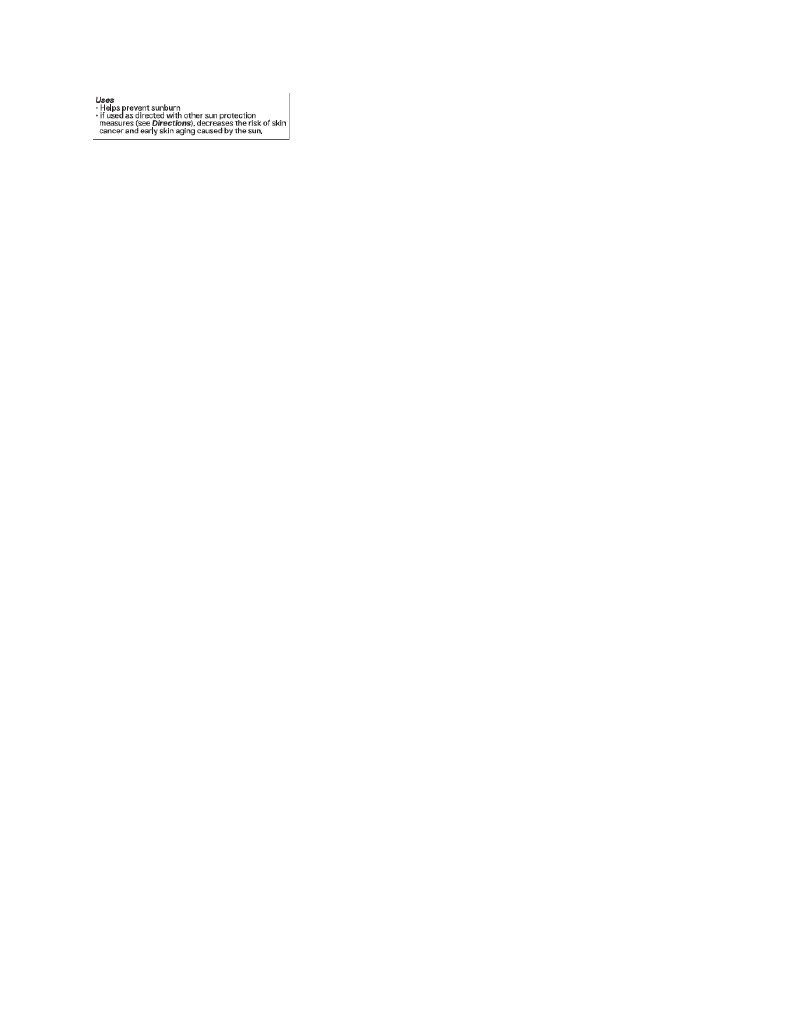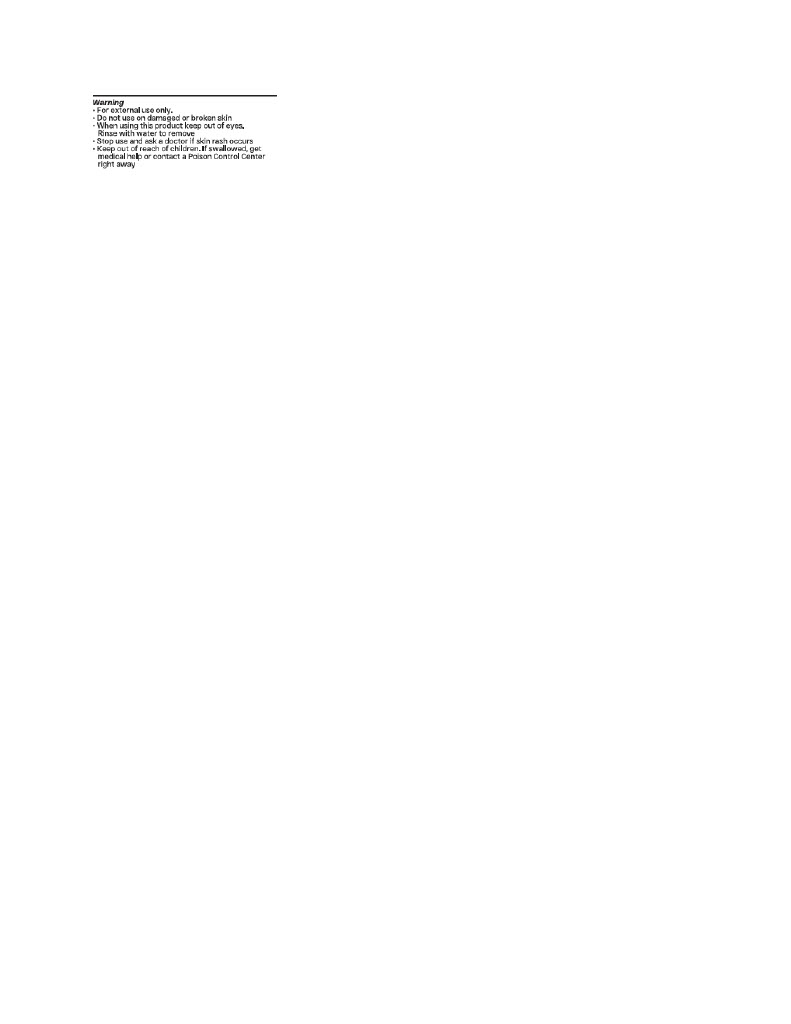 DRUG LABEL: Organys Derma Made
NDC: 83612-0403 | Form: LOTION
Manufacturer: Organys Beauty
Category: otc | Type: HUMAN OTC DRUG LABEL
Date: 20251009

ACTIVE INGREDIENTS: ZINC OXIDE 132 mg/1 mL
INACTIVE INGREDIENTS: POLYMETHYLSILSESQUIOXANE (4.5 MICRONS); PALMITOYL TETRAPEPTIDE-7; TRILAURETH-4 PHOSPHATE; BUTYLOCTYL SALICYLATE; OCTYLDODECYL NEOPENTANOATE; ISODODECANE; .ALPHA.-BISABOLOL, (+)-; LAURYL PEG-8 DIMETHICONE (300 CPS); ALKYL (C12-15) BENZOATE; ALLANTOIN; FERROSOFERRIC OXIDE; DIMETHICONE; SODIUM CHLORIDE; FERRIC OXIDE YELLOW; CAPRYLYL GLYCOL; HEXYLENE GLYCOL; FERRIC OXIDE RED; SODIUM HYDROXIDE; WATER; NIACINAMIDE; ETHYLHEXYLGLYCERIN; DIMETHICONOL/PROPYLSILSESQUIOXANE/SILICATE CROSSPOLYMER (450000000 MW); PROPANEDIOL; TETRASODIUM GLUTAMATE DIACETATE; PHENOXYETHANOL; .BETA.-TOCOPHEROL

Organys Derma Made